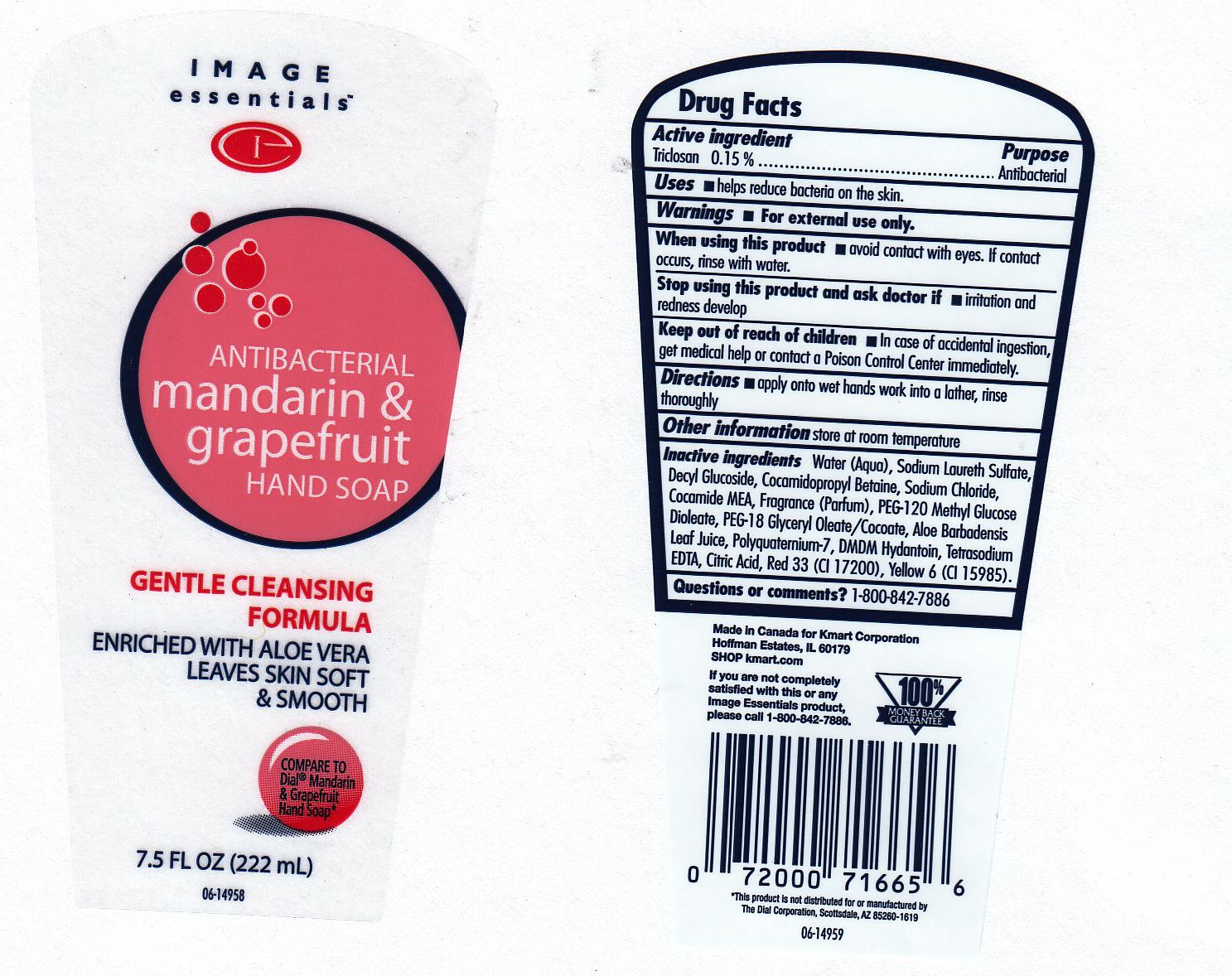 DRUG LABEL: Antibacterial Mandarin and Grapefruit Handsoap
NDC: 63148-215 | Form: LIQUID
Manufacturer: Apollo Health and Beauty Care
Category: otc | Type: HUMAN OTC DRUG LABEL
Date: 20100628

ACTIVE INGREDIENTS: TRICLOSAN 0.1500 mL/100 mL

ANTIBACTERIAL MANDARIN AND GRAPEFRUIT HAND SOAP

ACTIVE INGREDIENT

TRICLOSAN 0.15 % (ANTIBACTERIAL)

USES

HELPS REDUCE BACTERIA ON THE SKIN.

WARNINGS

FOR EXTERNAL USE ONLY.

WHEN USING THIS PRODUCT

AVOID CONTACT WITH EYES. IF CONTACT OCCURS, RINSE WITH WATER.

STOP USING THIS PRODUCT AND ASK DOCTOR IF

IRRITATION AND REDNESS DEVELOP

KEEP OUT OF REACH OF CHILDREN

IN CASE OF ACCIDENTAL INGESTION, GET MEDICAL HELP OR CONTACT A POISON CONTROL CENTER IMMEDIATELY.

QUESTION OR COMMENTS?

1 - 800 - 842 - 7886

FRONT AND BACK LABELS

8OZ FRONT AND BACK LABELS: IE8OZ.jpg